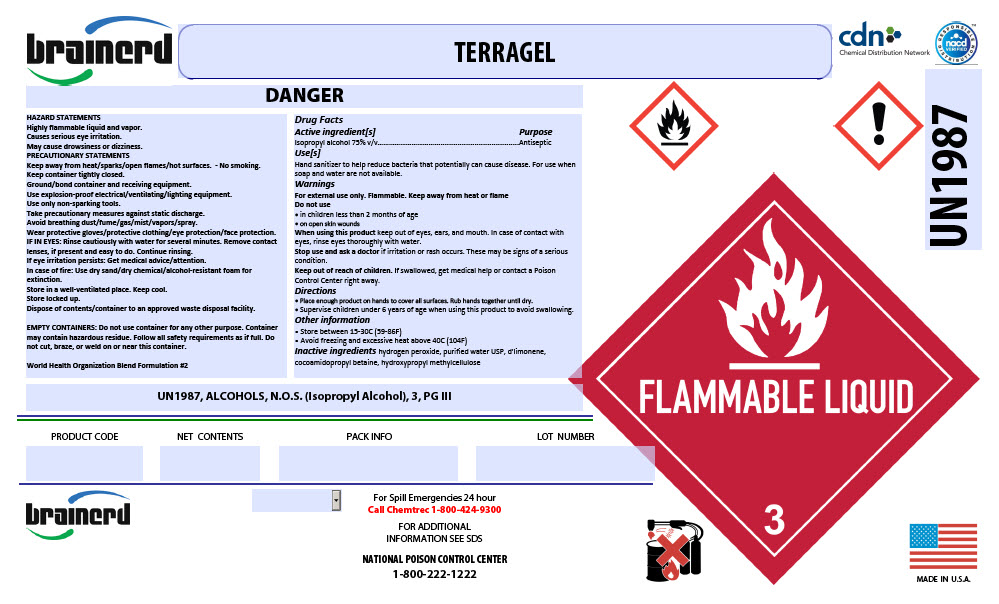 DRUG LABEL: Terragel
NDC: 54555-129 | Form: LIQUID
Manufacturer: Brainerd Chemical Company Inc.,
Category: otc | Type: HUMAN OTC DRUG LABEL
Date: 20200605

ACTIVE INGREDIENTS: alcohol 750 mL/1 L
INACTIVE INGREDIENTS: Cocamidopropyl Betaine; hydrogen peroxide; water; LIMONENE OXIDE, TRANS-(+)-; HYDROXYMETHYL CELLULOSE

Terragel

Drug Facts

Active ingredient[s]

Isopropyl alcohol 75% v/v

Purpose

Antiseptic

Use[s]

Hand sanitizer to help reduce bacteria that potentially can cause disease. For use when soap and water are not available.

Warnings

For external use only. Flammable. Keep away from heat or flame

Do not use

- in children less than 2 months of age
- on open skin wounds

When using this product keep out of eyes, ears, and mouth. In case of contact with eyes, rinse eyes thoroughly with water.

Stop use and ask a doctor if irritation or rash occurs. These may be signs of a serious condition.

Keep out of reach of children. If swallowed, get medical help or contact a Poison Control Center right away.

Directions

- Place enough product on hands to cover all surfaces. Rub hands together until dry.
- Supervise children under 6 years of age when using this product to avoid swallowing.

Other information

- Store between 15-30C (59-86F)
- Avoid freezing and excessive heat above 40C (104F)

Inactive ingredients

hydrogen peroxide, purified water USP, d'limonene, cocoamidopropyl betaine, hydroxypropyl methylcellulose

PRINCIPAL DISPLAY PANEL - 1320 Liter Tank Label

brainerd

TERRAGEL

Chemical Distribution Network

RESPONSIBLE
nacd
VERIFIED
DISTRIBUTION™

!
UN1987

FLAMMABLE LIQUID
3

MADE IN U.S.A.

DANGER

HAZARD STATEMENTS
Highly flammable liquid and vapor.
Causes serious eye irritation.
May cause drowsiness or dizziness.
PRECAUTIONARY STATEMENTS
Keep away from heat/sparks/open flames/hot surfaces. - No smoking.
Keep container tightly closed.
Ground/bond container and receiving equipment.
Use explosion-proof electrical/ventilating/lighting equipment.
Use only non-sparking tools.
Take precautionary measures against static discharge.
Avoid breathing dust/fume/gas/mist/vapors/spray.
Wear protective gloves/protective clothing/eye protection/face protection.
IF IN EYES: Rinse cautiously with water for several minutes. Remove contact
lenses, if present and easy to do. Continue rinsing.
If eye irritation persists: Get medical advice/attention.
In case of fire: Use dry sand/dry chemical/alcohol-resistant foam for
extinction.
Store in a well-ventilated place. Keep cool.
Store locked up.
Dispose of contents/container to an approved waste disposal facility.

EMPTY CONTAINERS: Do not use container for any other purpose. Container
may contain hazardous residue. Follow all safety requirements as if full. Do
not cut, braze, or weld on or near this container.

World Health Organization Blend Formulation #2

UN1987, ALCOHOLS, N.O.S. (Isopropyl Alcohol), 3, PG III

PRODUCT CODE

NET CONTENTS

PACK INFO

LOT NUMBER

For Spill Emergencies 24 hour
Call Chemtrec 1-800-424-9300

FOR ADDITIONAL
INFORMATION SEE SDS

NATIONAL POISON CONTROL CENTER
1-800-222-1222